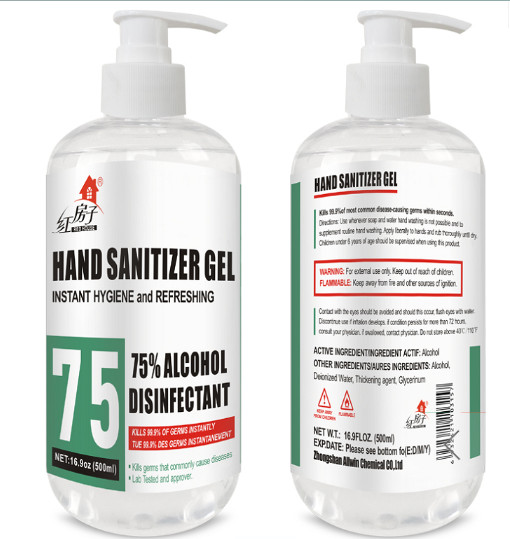 DRUG LABEL: 75% alcohol hand sanitizer gel
NDC: 67986-001 | Form: GEL
Manufacturer: Zhongshan Allwin Chemical Co., Ltd.
Category: otc | Type: HUMAN OTC DRUG LABEL
Date: 20200411

ACTIVE INGREDIENTS: ALCOHOL 375 mL/500 mL
INACTIVE INGREDIENTS: WATER; GLYCERIN

PURPOSE

Clean stains in hands

ACTIVE INGREDIENT

Alcohol

INACTIVE INGREDIENT

Deionized Water

glycerinum

keep out of children

DOSAGE AND ADMINISTRATION

Proper amount

INDICATIONS AND USAGE

Apply to palm and wash with water

WARNINGS

keep out of children